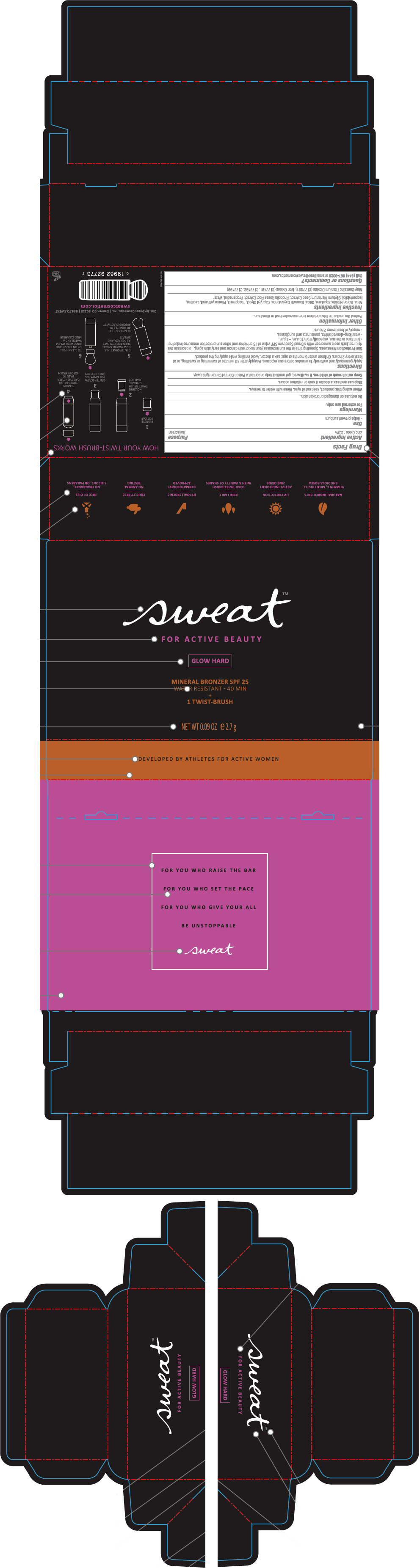 DRUG LABEL: Sweat Glow Hard Bronzer SPF 25
NDC: 80449-003 | Form: POWDER
Manufacturer: Sweat Cosmetics, Inc.
Category: otc | Type: HUMAN OTC DRUG LABEL
Date: 20200914

ACTIVE INGREDIENTS: Zinc Oxide 12 g/100 g
INACTIVE INGREDIENTS: Mica; Boron Nitride; Squalane; Silicon Dioxide; Bismuth Oxychloride; Caprylyl Glycol; Tocopherol; Phenoxyethanol; Isopentyldiol; Milk Thistle; Sedum Roseum Root; Propanediol; Water; Titanium Dioxide; Ferric Oxide Red; Ferric Oxide Yellow; Ferrosoferric Oxide

Sweat™ Glow Hard Bronzer SPF 25

Drug Facts

Active Ingredients

Zinc Oxide 12%

Purpose

Sunscreen

Use

Helps prevent sunburn

Warnings

For external use only.

Do not use on damaged or broken skin.

When using this product, keep out of eyes. Rinse with water to remove.

Stop use and ask doctor if rash or irritation occurs.

Keep out of reach of children. If swallowed, get medical help or contact a Poison Control Center right away.

Directions

Apply generously and uniformly 15 minutes before sun exposure. Reapply after 40 minutes of swimming or sweating, or at least every 2 hours. Children under 6 months of age: ask a doctor. Avoid inhaling while applying the product.

Sun Protection Measures. Spending time in the sun increases your risk of skin cancer and early skin aging. To decrease this risk, regularly use a sunscreen with a Broad Spectrum SPF value of 15 or higher and other sun protection measures including:

- limit time in the sun, especially from 10 a.m. - 2 p.m.
- wear long-sleeved shirts, pants, hats and sunglasses.
- reapply at least every 2 hours.

Other Information

Protect the product in this container from excessive heat or direct sun.

Inactive Ingredients

Mica, Boron Nitride, Squalane, Silica, Bismuth Oxychloride, Caprylyl Glycol, Tocopherol, Phenoxyethanol, Lecithin, Isopentyldiol, Silybum Marianum Seed Extract, Rhodiola Rosea Root Extract, Propanediol, Water

May Contain: Titanium Dioxide (Cl 77891), Iron Oxides (Cl 77491, Cl 77492, Cl 77499)

Questions or Comments?

Call (844) 867-9328 or email info@sweatcosmetics.com

Dist. by Sweat Cosmetics, Inc. | Denver, CO 80210

PRINCIPAL DISPLAY PANEL - 2.7 g Container Box

sweat™

FOR ACTIVE BEAUTY

GLOW HARD

MINERAL BRONZER SPF 25
WATER RESISTANT - 40 MIN
+
1 TWIST-BRUSH

NET WT 0.09 OZ e 2.7 g